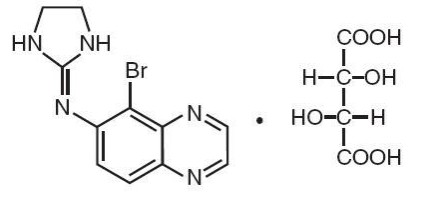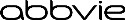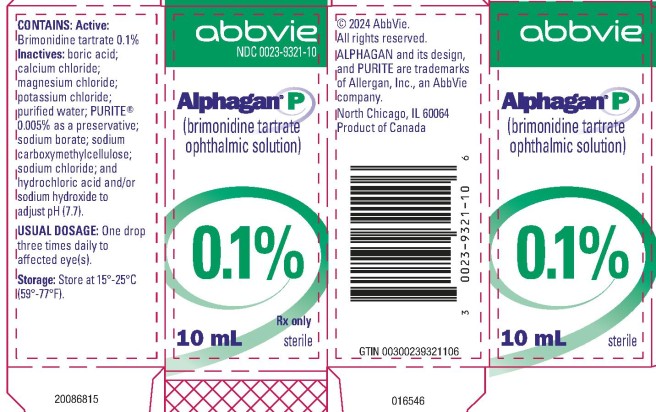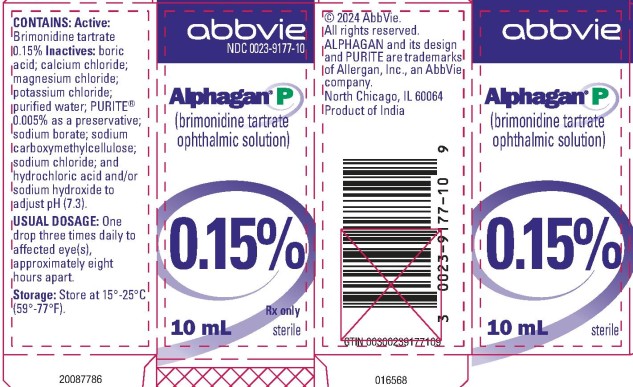 DRUG LABEL: ALPHAGAN P
NDC: 0023-9321 | Form: SOLUTION/ DROPS
Manufacturer: Allergan, Inc.
Category: prescription | Type: HUMAN PRESCRIPTION DRUG LABEL
Date: 20250918

ACTIVE INGREDIENTS: BRIMONIDINE TARTRATE 1 mg/1 mL
INACTIVE INGREDIENTS: BORIC ACID; CALCIUM CHLORIDE; MAGNESIUM CHLORIDE; POTASSIUM CHLORIDE; WATER; SODIUM BORATE; CARBOXYMETHYLCELLULOSE SODIUM, UNSPECIFIED; SODIUM CHLORIDE; HYDROCHLORIC ACID; SODIUM HYDROXIDE; SODIUM CHLORITE

HIGHLIGHTS OF PRESCRIBING INFORMATION

These highlights do not include all the information needed to use ALPHAGAN P safely and effectively. See full prescribing information for ALPHAGAN P.
ALPHAGAN® P (brimonidine tartrate ophthalmic solution) 0.1% and 0.15%, for topical ophthalmic use
Initial U.S. Approval: 1996

RECENT MAJOR CHANGES

Warnings and Precautions (5.3) 9/2025

1 INDICATIONS AND USAGE

ALPHAGAN P is an alpha adrenergic agonist indicated for the reduction of elevated intraocular pressure (IOP) in patients with open-angle glaucoma or ocular hypertension. (1)

2 DOSAGE AND ADMINISTRATION

One drop in the affected eye(s) three times daily, approximately 8 hours apart. (2)

3 DOSAGE FORMS AND STRENGTHS

Ophthalmic solution containing 0.1% (1 mg/mL) or 0.15% (1.5 mg/mL) brimonidine tartrate. (3)

4 CONTRAINDICATIONS

- Neonates and infants (pediatric patients younger than 2 years old). (4.1)
- Hypersensitivity Reactions. (4.2)

5 WARNINGS AND PRECAUTIONS

Potentiation of vascular insufficiency. (5.1)

6 ADVERSE REACTIONS

Most common adverse reactions occurring in approximately 5% to 20% of patients receiving brimonidine ophthalmic solution (0.1% to 0.2%) included allergic conjunctivitis, burning sensation, conjunctival folliculosis, conjunctival hyperemia, eye pruritus, hypertension, ocular allergic reaction, oral dryness, and visual disturbance. (6.1)

To report SUSPECTED ADVERSE REACTIONS, contact AbbVie at 1-800-678-1605 or the FDA at 1-800-FDA-1088 or www.fda.gov/medwatch.

7 DRUG INTERACTIONS

- Antihypertensives/cardiac glycosides may lower blood pressure. (7.1)
- Use with CNS depressants may result in an additive or potentiating effect. (7.2)
- Tricyclic antidepressants may potentially blunt the hypotensive effect of systemic clonidine. (7.3)
- Monoamine oxidase inhibitors may result in increased hypotension. (7.4)

8 USE IN SPECIFIC POPULATIONS

Use with caution in pediatric patients aged 2 years and older. (8.4)

FULL PRESCRIBING INFORMATION

1 INDICATIONS AND USAGE

ALPHAGAN P (brimonidine tartrate ophthalmic solution) 0.1% or 0.15% is indicated for the reduction of elevated intraocular pressure (IOP) in patients with open-angle glaucoma or ocular hypertension.

2 DOSAGE AND ADMINISTRATION

The recommended dosage is one drop of ALPHAGAN P in the affected eye(s) three times daily, approximately 8 hours apart. ALPHAGAN P may be used concomitantly with other topical ophthalmic drug products to lower intraocular pressure. If more than one topical ophthalmic product is to be used, the different products should be instilled at least 5 minutes apart.

3 DOSAGE FORMS AND STRENGTHS

Ophthalmic solution containing 0.1% (1 mg/mL) or 0.15% (1.5 mg/mL) brimonidine tartrate.

4 CONTRAINDICATIONS

4.1 Neonates and Infants (Pediatric Patients Younger than 2 Years Old)

ALPHAGAN P is contraindicated in neonates and infants (pediatric patients younger than 2 years old) [see Use in Specific Populations (8.4)].

4.2 Hypersensitivity Reactions

ALPHAGAN P is contraindicated in patients who have exhibited a hypersensitivity reaction to any component of this medication in the past.

5 WARNINGS AND PRECAUTIONS

5.1 Potentiation of Vascular Insufficiency

ALPHAGAN P may potentiate syndromes associated with vascular insufficiency. ALPHAGAN P should be used with caution in patients with depression, cerebral or coronary insufficiency, Raynaud’s phenomenon, orthostatic hypotension, or thromboangiitis obliterans.

5.2 Severe Cardiovascular Disease

Although brimonidine tartrate ophthalmic solution had minimal effect on the blood pressure of patients in clinical studies, caution should be exercised in treating patients with severe cardiovascular disease.

5.3 Contamination of Topical Ophthalmic Products After Use

There have been reports of bacterial keratitis associated with the use of multiple-dose containers of topical ophthalmic products. These containers had been inadvertently contaminated by patients who, in most cases, had a concurrent corneal disease or a disruption of the ocular epithelial surface. Do not touch the tip of the dispensing container to the eye or surrounding structures. Serious damage to the eye and subsequent loss of vision may result from using contaminated solutions [see Patient Counseling Information (17)].

6 ADVERSE REACTIONS

The following serious adverse reactions are described elsewhere in the labeling:

- Potentiation of Vascular Insufficiency [see Warnings and Precautions (5.1)]
- Severe Cardiovascular Disease [see Warnings and Precautions (5.2)]
- Contamination of Topical Ophthalmic Products after Use [see Warnings and Precautions (5.3)]
- Neonates and Infants (Pediatric Patients Younger than 2 Years Old) [see Contraindications (4.1)]

6.1 Clinical Trials Experience

Because clinical trials are conducted under widely varying conditions, adverse reaction rates observed in the clinical trials of a drug cannot be directly compared to rates in the clinical trials of another drug and may not reflect the rates observed in practice.

Adverse reactions occurring in approximately 10% to 20% of the subjects receiving brimonidine ophthalmic solution (0.1% to 0.2%) included: allergic conjunctivitis, conjunctival hyperemia, and eye pruritus. Adverse reactions occurring in approximately 5% to 9% included: burning sensation, conjunctival folliculosis, hypertension, ocular allergic reaction, oral dryness, and visual disturbance.

Adverse reactions occurring in approximately 1% to 4% of the subjects receiving brimonidine ophthalmic solution (0.1% to 0.2%) included: abnormal taste, allergic reaction, asthenia, blepharitis, blepharoconjunctivitis, blurred vision, bronchitis, cataract, conjunctival edema, conjunctival hemorrhage, conjunctivitis, cough, dizziness, dyspepsia, dyspnea, epiphora, eye discharge, eye dryness, eye irritation, eye pain, eyelid edema, eyelid erythema, fatigue, flu syndrome, follicular conjunctivitis, foreign body sensation, gastrointestinal disorder, headache, hypercholesterolemia, hypotension, infection (primarily colds and respiratory infections), insomnia, keratitis, lid disorder, pharyngitis, photophobia, rash, rhinitis, sinus infection, sinusitis, somnolence, stinging, superficial punctate keratopathy, tearing, visual field defect, vitreous detachment, vitreous disorder, vitreous floaters, and worsened visual acuity.

The following reactions were reported in less than 1% of subjects: corneal erosion, hordeolum, nasal dryness, and taste perversion.

6.2 Postmarketing Experience

The following reactions have been identified during postapproval use of brimonidine tartrate ophthalmic solutions. Because these reactions are reported voluntarily from a population of uncertain size, it is not always possible to reliably estimate their frequency or establish a causal relationship to drug exposure.

- Bradycardia, depression, hypersensitivity, iritis, keratoconjunctivitis sicca, miosis, nausea, skin reactions (including erythema, eyelid pruritus, rash, and vasodilation), syncope, and tachycardia.
- Apnea, coma, hypotension, hypothermia, hypotonia, lethargy, pallor, respiratory depression, and somnolence have been reported in infants receiving brimonidine tartrate ophthalmic solutions.

7 DRUG INTERACTIONS

7.1 Antihypertensives/Cardiac Glycosides

Because ALPHAGAN P may reduce blood pressure, caution in using drugs such as antihypertensives and/or cardiac glycosides with ALPHAGAN P is advised.

7.2 CNS Depressants

Although specific drug interaction studies have not been conducted with ALPHAGAN P, the possibility of an additive or potentiating effect with CNS depressants (alcohol, barbiturates, opiates, sedatives, or anesthetics) should be considered.

7.3 Tricyclic Antidepressants

Tricyclic antidepressants have been reported to blunt the hypotensive effect of systemic clonidine. It is not known whether the concurrent use of these agents with ALPHAGAN P in humans can lead to resulting interference with the IOP lowering effect. Caution is advised in patients taking tricyclic antidepressants which can affect the metabolism and uptake of circulating amines.

7.4 Monoamine Oxidase Inhibitors

Monoamine oxidase (MAO) inhibitors may theoretically interfere with the metabolism of brimonidine and potentially result in an increased systemic side-effect such as hypotension. Caution is advised in patients taking MAO inhibitors which can affect the metabolism and uptake of circulating amines.

8 USE IN SPECIFIC POPULATIONS

8.1 Pregnancy

Risk Summary

There are no adequate and well-controlled studies with ALPHAGAN P in pregnant women. In the U.S. general population, the estimated background risk of major birth defects and miscarriage in clinically recognized pregnancies is 2% to 4% and 15% to 20%, respectively.

In animal studies, brimonidine crossed the placenta and entered into the fetal circulation to a limited extent (see Data). Because animal reproduction studies are not always predictive of human response, ALPHAGAN P should be used during pregnancy only if the potential benefit to the mother justifies the potential risk to the fetus.

Data

Human Data

Limited available data from postmarketing safety reports and published literature with topical use of brimonidine ophthalmic solution in pregnant women are insufficient to inform a drug-associated risk of pregnancy-related adverse outcomes including miscarriage, stillbirth, congenital anomaly, and events experienced by offspring while breastfeeding.

Animal Data

Embryofetal studies were conducted in pregnant rabbits administered brimonidine tartrate by daily oral gavage on gestation days 6 to 18, to target the period of organogenesis. Brimonidine caused miscarriage at 5 mg/kg/day (approximately 70- or 50-times the recommended human ophthalmic dose [RHOD] based on AUC, respectively for brimonidine tartrate 0.1% and 0.15%). The no observed adverse effect level (NOAEL) for developmental toxicity in rabbits was 1 mg/kg/day (approximately 9- and 6-fold the RHOD based on AUC, respectively for brimonidine tartrate 0.1% and 0.15%). No treatment-related malformations were observed in rabbits. Signs of maternal sedation and fatigue were observed at all dose levels; the lowest observed adverse effect level (LOAEL) for maternal toxicity was 5 mg/kg/day, based on the dose response for these signs.

Embryofetal studies were conducted in pregnant rats administered brimonidine tartrate by daily oral gavage on gestation days 6 to 15, to target the period of organogenesis. The NOAEL for developmental toxicity was 2.5 mg/kg/day (approximately 1100- and 750-fold the RHOD based on AUC, respectively for brimonidine tartrate 0.1% and 0.15%). No treatment-related malformations were observed in rats. The LOAEL for maternal toxicity was 2.5 mg/kg/day, based on signs of sedation and fatigue. The maternal NOAEL was 1.0 mg/kg/day (250- and 180-fold the RHOD based on AUC, respectively for brimonidine tartrate 0.1% and 0.15%).

After pregnant rats received a single oral dose of ^14C-brimonidine tartrate, brimonidine and metabolites crossed the placenta and were detectable in fetal blood and organs.

8.2 Lactation

Risk Summary

It is not known whether brimonidine tartrate is excreted in human milk. In animal studies, brimonidine tartrate has been shown to cross the blood-brain barrier and is excreted into breast milk after oral administration to lactating rats (see Data). Because of the potential for serious adverse reactions, including central nervous system depression and apnea, from ALPHAGAN P in nursing infants, ALPHAGAN P is not recommended for use during lactation.

Data

Animal Data

After a single oral dose of ^14C-labeled brimonidine tartrate to lactating rats, brimonidine and metabolites were detected in milk. After male and female rats received a single oral dose of ^14C-brimonidine tartrate, brimonidine crossed the blood-brain barrier. Radiolabel was detected in the cerebellum, cerebrum, and spinal cord.

8.4 Pediatric Use

ALPHAGAN P is contraindicated in pediatric patients younger than 2 years old [see Contraindications (4.1)]. During postmarketing surveillance, apnea, bradycardia, coma, hypotension, hypothermia, hypotonia, lethargy, pallor, respiratory depression, and somnolence have been reported in infants receiving brimonidine.

In a well-controlled clinical study conducted in pediatric glaucoma patients aged 2 to 7 years old, the most commonly observed adverse reactions with brimonidine tartrate ophthalmic solution 0.2% dosed three times daily were somnolence (50% to 83% in pediatric patients aged 2 to 6 years old) and decreased alertness. In pediatric patients aged 7 years and older (greater than 20 kg), somnolence appears to occur less frequently (25%). Approximately 16% of pediatric patients on brimonidine tartrate ophthalmic solution 0.2% discontinued from the study due to somnolence.

8.5 Geriatric Use

No overall differences in safety or effectiveness have been observed between elderly and other adult patients.

10 OVERDOSAGE

Limited information exists on accidental ingestion of brimonidine in adults; the only adverse reaction reported to date has been hypotension. Symptoms of brimonidine overdose have been reported in neonates, infants, and children receiving ALPHAGAN P as part of medical treatment of congenital glaucoma or by accidental oral ingestion [see Use in Specific Populations (8.4)]. Treatment of an oral overdose includes supportive and symptomatic therapy; a patent airway should be maintained.

11 DESCRIPTION

ALPHAGAN P (brimonidine tartrate ophthalmic solution) 0.1% or 0.15%, sterile, is a relatively selective alpha-2 adrenergic receptor agonist for topical ophthalmic use.

The structural formula of brimonidine tartrate is:

5-Bromo-6-(2-imidazolidinylideneamino) quinoxaline L-tartrate; MW= 442.24

In solution, ALPHAGAN P (brimonidine tartrate ophthalmic solution) has a clear, greenish-yellow color. It has an osmolality of 250-350 mOsmol/kg and a pH of 7.4-8.0 (0.1%) or 6.9-7.4 (0.15%).

Brimonidine tartrate appears as an off-white to pale-yellow powder and is soluble in both water (0.6 mg/mL) and in the product vehicle (1.4 mg/mL) at pH 7.7.

Each mL of ALPHAGAN P contains the active ingredient brimonidine tartrate 0.1% (1 mg/mL) or 0.15% (1.5 mg/mL) with the inactive ingredients sodium carboxymethylcellulose; sodium borate; boric acid; sodium chloride; potassium chloride; calcium chloride; magnesium chloride; PURITE® 0.005% (0.05 mg/mL) as a preservative; purified water; and hydrochloric acid and/or sodium hydroxide to adjust pH.

12 CLINICAL PHARMACOLOGY

12.1 Mechanism of Action

ALPHAGAN P is a relatively selective alpha-2 adrenergic receptor agonist with a peak ocular hypotensive effect occurring at two hours post-dosing.

Fluorophotometric studies in animals and humans suggest that brimonidine tartrate has a dual mechanism of action by reducing aqueous humor production and increasing uveoscleral outflow.

12.3 Pharmacokinetics

Absorption

After ocular administration of either a 0.1% or 0.2% solution, plasma concentrations peaked within 0.5 to 2.5 hours and declined with a systemic half-life of approximately 2 hours.

Distribution

Brimonidine was approximately 29% bound to plasma proteins in healthy subjects.

Elimination

Metabolism

In humans, brimonidine is extensively metabolized by the liver.

Excretion

Urinary excretion is the major route of elimination of brimonidine and its metabolites. Approximately 87% of an orally-administered radioactive dose of brimonidine was eliminated within 120 hours, with 74% found in the urine.

13 NONCLINICAL TOXICOLOGY

13.1 Carcinogenesis, Mutagenesis, Impairment of Fertility

Carcinogenesis

No compound-related carcinogenic effects were observed in either mice or rats following a 21-month and 24-month study, respectively. In these studies, dietary administration of brimonidine tartrate at doses up to 2.5 mg/kg/day in mice and 1 mg/kg/day in rats achieved approximately 150 and 120 times or 93 and 76 times the recommended human ophthalmic dose (RHOD) based on Cmax respectively for brimonidine tartrate 0.1% or 0.15%.

Mutagenesis

Brimonidine tartrate was not mutagenic or clastogenic in a series of in vitro and in vivo studies including the Ames bacterial reversion test, chromosomal aberration assay in Chinese Hamster Ovary (CHO) cells, and three in vivo studies in CD-1 mice: a host-mediated assay, cytogenetic study, and dominant lethal assay.

Impairment of Fertility

A reproduction and fertility study in rats with brimonidine tartrate demonstrated no adverse effect on male or female fertility at oral doses up to 1 mg/kg (approximately 250 or 180 times the recommended human ophthalmic dose [RHOD] based on estimated AUC) respectively for brimonidine tartrate 0.1% and 0.15%.

14 CLINICAL STUDIES

Elevated IOP presents a major risk factor in glaucomatous field loss. The higher the level of IOP, the greater the likelihood of optic nerve damage and visual field loss. Brimonidine tartrate has the action of lowering intraocular pressure with minimal effect on cardiovascular and pulmonary parameters.

Clinical studies were conducted to evaluate the safety, efficacy, and acceptability of ALPHAGAN P (brimonidine tartrate ophthalmic solution) 0.15% compared with ALPHAGAN administered three-times-daily in patients with open-angle glaucoma or ocular hypertension. Those results indicated that ALPHAGAN P (brimonidine tartrate ophthalmic solution) 0.15% is comparable in IOP lowering effect to ALPHAGAN (brimonidine tartrate ophthalmic solution) 0.2%, and effectively lowers IOP in patients with open-angle glaucoma or ocular hypertension by approximately 2-6 mmHg.

A clinical study was conducted to evaluate the safety, efficacy, and acceptability of ALPHAGAN P (brimonidine tartrate ophthalmic solution) 0.1% compared with ALPHAGAN administered three-times-daily in patients with open-angle glaucoma or ocular hypertension. Those results indicated that ALPHAGAN P (brimonidine tartrate ophthalmic solution) 0.1% is equivalent in IOP lowering effect to ALPHAGAN (brimonidine tartrate ophthalmic solution) 0.2%, and effectively lowers IOP in patients with open-angle glaucoma or ocular hypertension by approximately 2-6 mmHg.

16 HOW SUPPLIED/STORAGE AND HANDLING

ALPHAGAN P is supplied sterile, in teal opaque plastic LDPE bottles and tips, with purple high impact polystyrene (HIPS) caps as follows:

0.1%

5 mL in 10 mL bottle NDC 0023-9321-05

10 mL in 10 mL bottle NDC 0023-9321-10

15 mL in 15 mL bottle NDC 0023-9321-15

0.15%

5 mL in 10 mL bottle NDC 0023-9177-05

10 mL in 10 mL bottle NDC 0023-9177-10

15 mL in 15 mL bottle NDC 0023-9177-15

Storage: Store at 15oC to 25oC (59oF to 77oF).

17 PATIENT COUNSELING INFORMATION

Handling the Container

Instruct patients that ocular solutions, if handled improperly or if the tip of the dispensing container contacts the eye or surrounding structures, can become contaminated by common bacteria known to cause ocular infections. Serious damage to the eye and subsequent loss of vision may result from using contaminated solutions [see Warnings and Precautions (5.3)]. Always replace the cap after using. If solution changes color or becomes cloudy, do not use. Do not use the product after the expiration date marked on the bottle.

When to Seek Physician Advice

Advise patients that if they have ocular surgery or develop an intercurrent ocular condition (e.g., trauma or infection), they should immediately seek their physician's advice concerning the continued use of the present multidose container.

Use with Other Ophthalmic Drugs

Advise patients that if more than one topical ophthalmic drug is being used, the drugs should be administered at least five minutes apart.

Potential for Decreased Mental Alertness

As with other similar medications, ALPHAGAN P may cause fatigue and/or drowsiness in some patients. Caution patients who engage in hazardous activities of the potential for a decrease in mental alertness.

Distributed by:
AbbVie Inc.
North Chicago, IL 60064

© 2025 AbbVie. All rights reserved.
ALPHAGAN P and its design and PURITE are trademarks of Allergan, Inc., an AbbVie company.

20091160

PRINCIPAL DISPLAY PANEL

abbvie
NDC 0023-9321-10
Alphagan® P
(brimonidine tartrate
ophthalmic solution)
0.1%
10 mL
Rx only
sterile

PRINCIPAL DISPLAY PANEL

abbvie
NDC 0023-9177-10
Alphagan® P
(brimonidine tartrate
ophthalmic solution)
0.15%
10 mL
Rx only
sterile